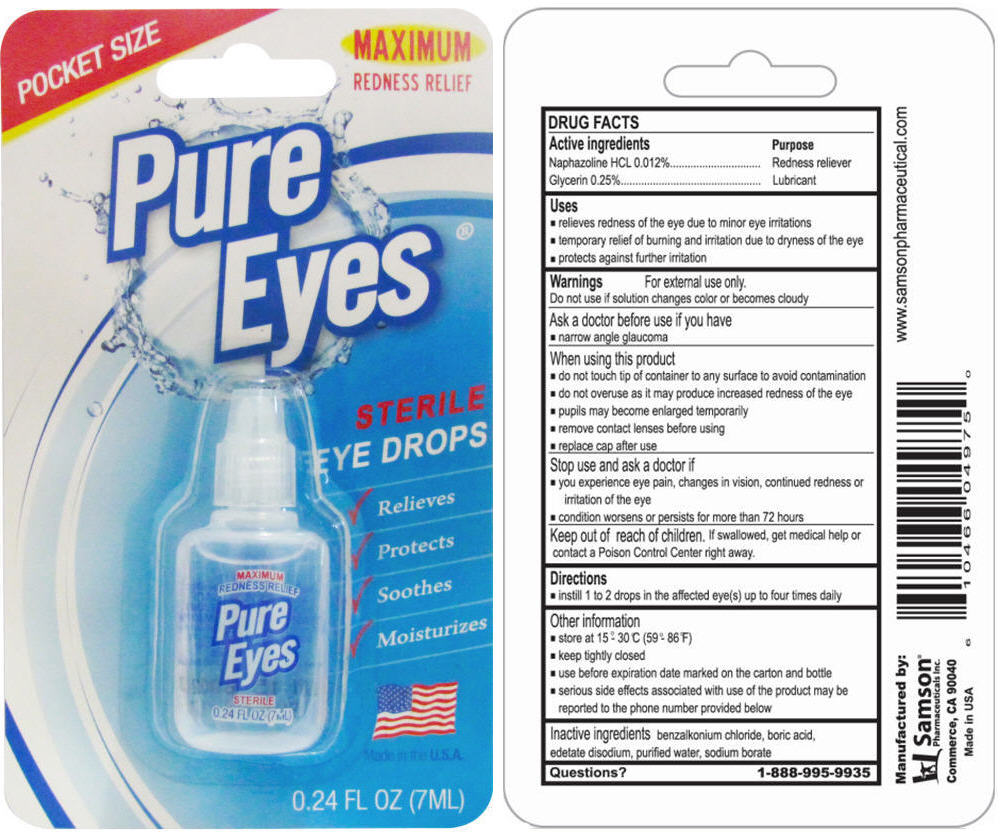 DRUG LABEL: Pure Eyes Sterile Eyes
NDC: 20146-7000 | Form: SOLUTION/ DROPS
Manufacturer: SAMSON PHARMACEUTICAL
Category: otc | Type: HUMAN OTC DRUG LABEL
Date: 20220131

ACTIVE INGREDIENTS: Naphazoline Hydrochloride 0.1 mg/1 mL; Glycerin 2.5 mg/1 mL
INACTIVE INGREDIENTS: benzalkonium chloride; boric acid; edetate disodium; water; sodium borate

Pure Eyes® Sterile Eyes

DRUG FACT

ACTIVE INGREDIENT

ACTIVE INGREDIENTS | PURPOSE
Naphazoline HCL 0.01% | Redness reliever
Glycerin 0.25% | Lubricant

Uses

♦ Relieve redness of the eye due to minor irritation
♦ Temporary relief of burning and irritation due to dryness of the eye
♦ Protects against further irritation

Warnings

For external use only

Do not use if solution changes color or becomes cloudy

Ask a doctor before use if you have

♦ Narrow angle glaucoma

When using this product

♦ Do not touch tip of container to any surface to avoid contamination
♦ Do not overuse as it may products increased redness of the eye
♦ Pupils may be come enlarged temporarily
♦ Remove contact lenses before using
♦ Replace cap after use

Stop use and ask a doctor if

♦ You experience eye pain, changes in vision, continued redness or irritation of the eyes
♦ Conditions worsens or persists for more than 72 hours

KEEP OUT OF REACH OF CHILDREN

Keep put of reach of children. Id swallowed, get medical help or contact a Poison Control Center right away.

Directions

♦ Instill 1 to 2 drops in the affected eye(s) up to 4 times daily

Other information

♦ Store at 15- 30 C (59-86 F)
♦ Keep tightly closed
♦ Use before expiration date marked on the carton and bottle
♦ Serious side effect associated with use of the product may be reported to the phone number provided below

Inactive ingredients

benzalkonium chloride, boric acid, edetate disodium, purified water, sodium borate.

Question?

1-888-995-9935

Manufactured by:
Samson Pharmaceutical
Commerce, CA 90040
Made in USA

PRINCIPAL DISPLAY PANEL - 7 mL Bottle Blister Pack

POCKET SIZE

MAXIMUM
REDNESS RELIEF

Pure
Eyes®

STERILE
EYE DROPS

✓ Relieves
✓ Protects
✓ Soothes
✓ Moisturizes

Made in the U.S.A.

0.24 FL OZ (7ML)